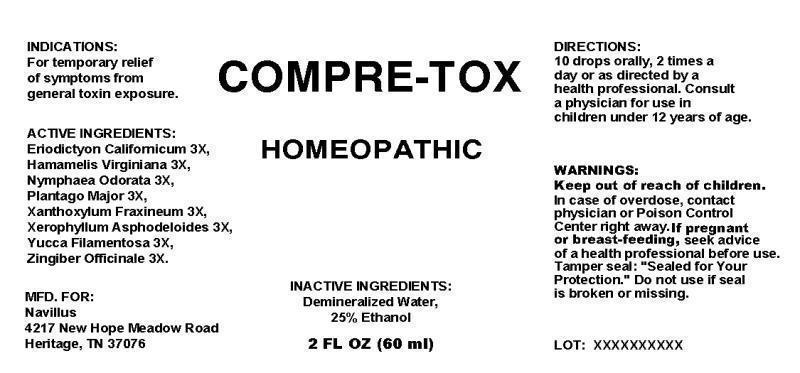 DRUG LABEL: Compre Tox
NDC: 43965-0001 | Form: LIQUID
Manufacturer: Kevin Sullivan  Navillus
Category: homeopathic | Type: HUMAN OTC DRUG LABEL
Date: 20121023

ACTIVE INGREDIENTS: ERIODICTYON CALIFORNICUM LEAF 3 [hp_X]/1 mL; HAMAMELIS VIRGINIANA ROOT BARK/STEM BARK 3 [hp_X]/1 mL; NYMPHAEA ODORATA ROOT 3 [hp_X]/1 mL; PLANTAGO MAJOR 3 [hp_X]/1 mL; ZANTHOXYLUM AMERICANUM BARK 3 [hp_X]/1 mL; XEROPHYLLUM ASPHODELOIDES 3 [hp_X]/1 mL; YUCCA FILAMENTOSA 3 [hp_X]/1 mL; GINGER 3 [hp_X]/1 mL
INACTIVE INGREDIENTS: WATER; ALCOHOL

Drug Facts

ACTIVE INGREDIENTS

Eriodictyon Californicum 3X, Hamamelis Virginiana 3X, Nymphaea Odorata 3X, Plantago Major 3X, Xanthoxylum Fraxineum 3X, Xerophyllum Asphodeloides 3X, Yucca Filamentosa 3X, Zingiber Officinale 3X.

INDICATIONS

For temporary relief of symptoms from general toxin exposure.

WARNINGS

Keep out of reach of children. In case of overdose, contact physician or Poison Control Center right away. If pregnant or breast-feeding, seek advice of a health professional before use. Tamper seal: "Sealed for Your Protection." Do not use if seal is broken or missing.

DIRECTIONS

10 drops orally, 2 times a day or as directed by a health professional. Consult a physician for use in children under 12 years of age.

INACTIVE INGREDIENTS

Demineralized Water, 25% Ethanol.

KEEP OUT OF REACH OF CHILDREN

In case of overdose, contact physician or Poison Control Center right away.

INDICATIONS AND USAGE

For temporary relief of symptoms from general toxin exposure.

QUESTIONS

MFD. FOR:

Navillus

4217 New Hope Meadow Road

Heritage, TN 37076

PACKAGE LABEL

COMPRE TOX

HOMEOPATHIC

2 FL OZ (60 ml)